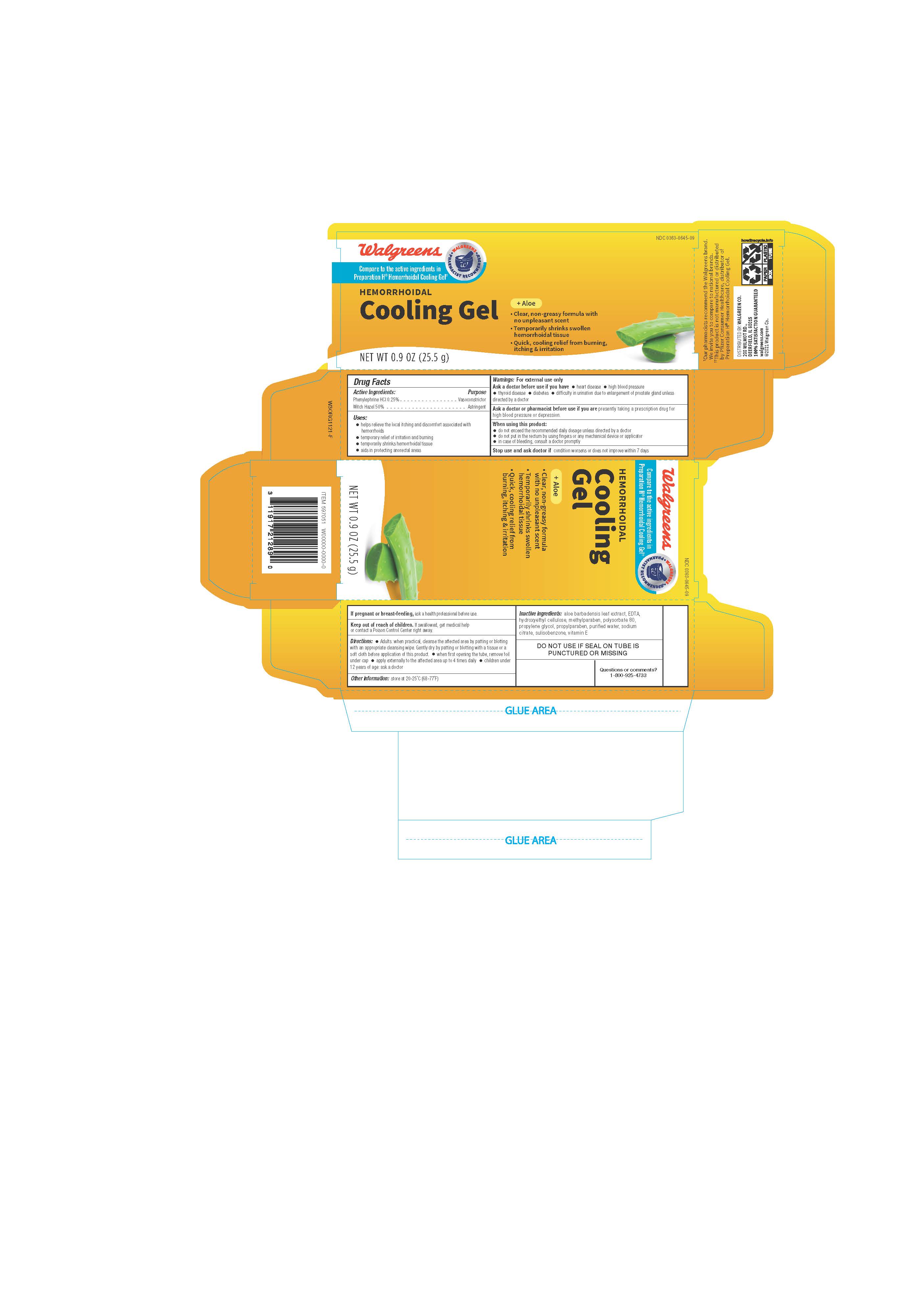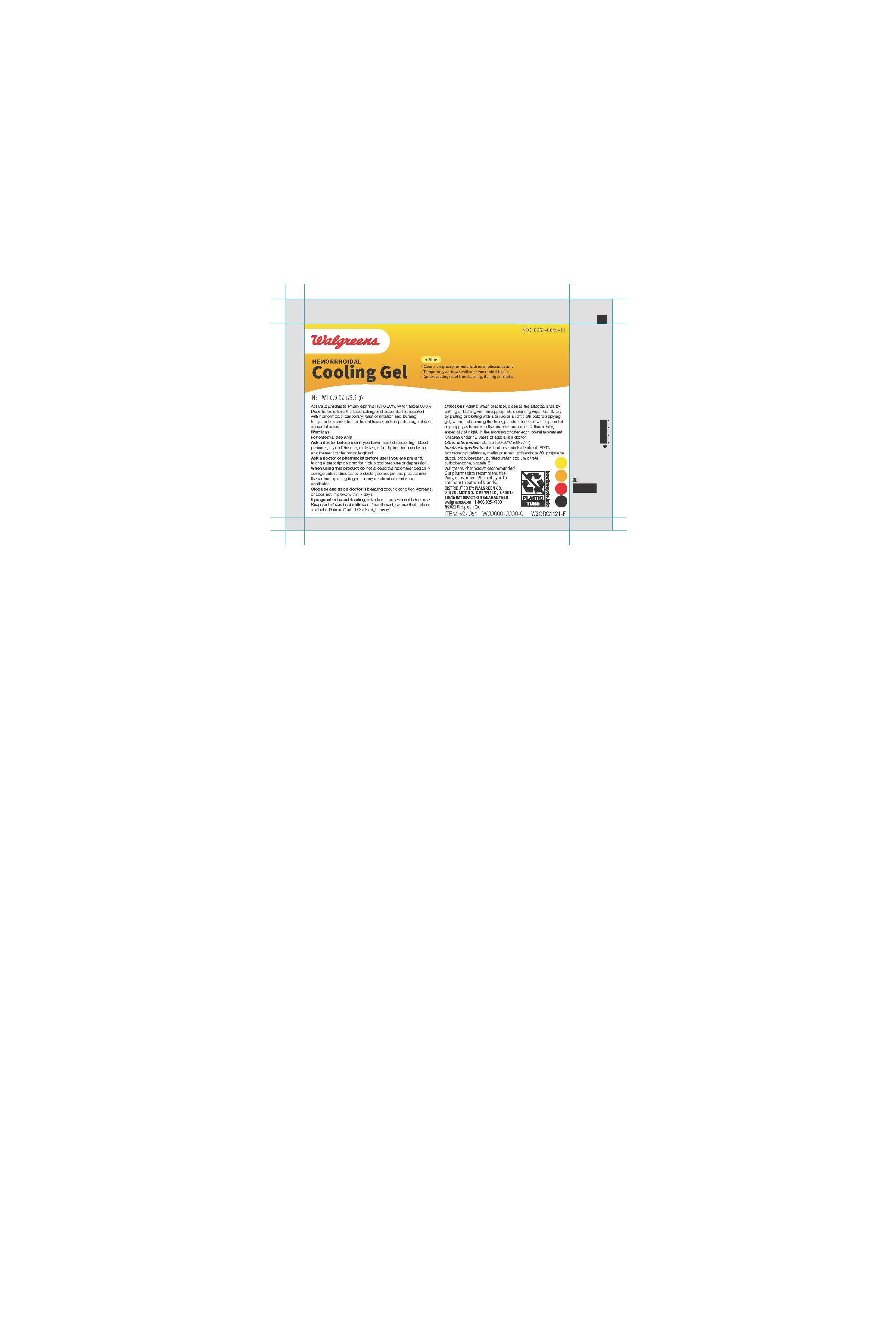 DRUG LABEL: Walgreens
NDC: 0363-6502 | Form: GEL
Manufacturer: Walgreens
Category: otc | Type: HUMAN OTC DRUG LABEL
Date: 20260115

ACTIVE INGREDIENTS: PHENYLEPHRINE HYDROCHLORIDE 2.5 mg/1 g; WITCH HAZEL 500 mg/1 g
INACTIVE INGREDIENTS: WATER; PROPYLENE GLYCOL; HYDROXYETHYL CELLULOSE, UNSPECIFIED; POLYSORBATE 80; SULISOBENZONE; TRISODIUM CITRATE DIHYDRATE; METHYLPARABEN; PROPYLPARABEN; ALOE VERA LEAF; EDETATE DISODIUM; ALPHA-TOCOPHEROL ACETATE

Walgreens®Hemorrhoidal Cooling Gel

Active ingredients

Phenylephrine HCl 0.25%

Witch hazel 50.0%

Purposes

Vasoconstrictor

Astringent

Uses

- helps relieve the local itching and discomfort associated with hemorrhoids
- temporary relief of irritation and burning
- temporarily shrinks hemorrhoidal tissue
- aids in protecting irritated anorectal areas

Warnings

For external use only

Ask a doctor before use if you have

- heart disease
- high blood pressure
- thyroid disease
- diabetes
- difficulty in urination due to enlargement of the prostate gland

Ask a doctor or pharmacist before use if you are

presently taking a prescription drug for high blood pressure or depression.

When using this product

- do not exceed the recommended daily dosage unless directed by a doctor
- do not put this product into the rectum by using fingers or any mechanical device or applicator
- in case of bleeding, consult a doctor promptly

Stop use and ask a doctor if

condition worsens or does not improve within 7 days

If pregnant or breast-feeding,

ask a health professional before use.

Keep out of reach of children.

If swallowed, get medical help or contact a Poison Control Center right away.

Directions:

- adults: when practical, cleanse the affected area by patting or blotting with an appropriate cleansing wipe. Gently dry by patting or blotting with a tissue or a soft cloth before applying gel.
- when first opening the tube, puncture foil seal with top end of cap
- apply externally to the affected area up to 4 times daily, especially at night, in the morning or after each bowel movement
- children under 12 years of age: ask a doctor

Other information

store at 20-25°C (68-77°F)

Inactive ingredients

aloe barbadensis leaf extract, EDTA, hydroxyethyl cellulose, methylparaben, polysorbate 80, propylene glycol, propylparaben, purified water, sodium citrate, sulisobenzone, vitamin E

Questions or comments?

1-800-925-4733